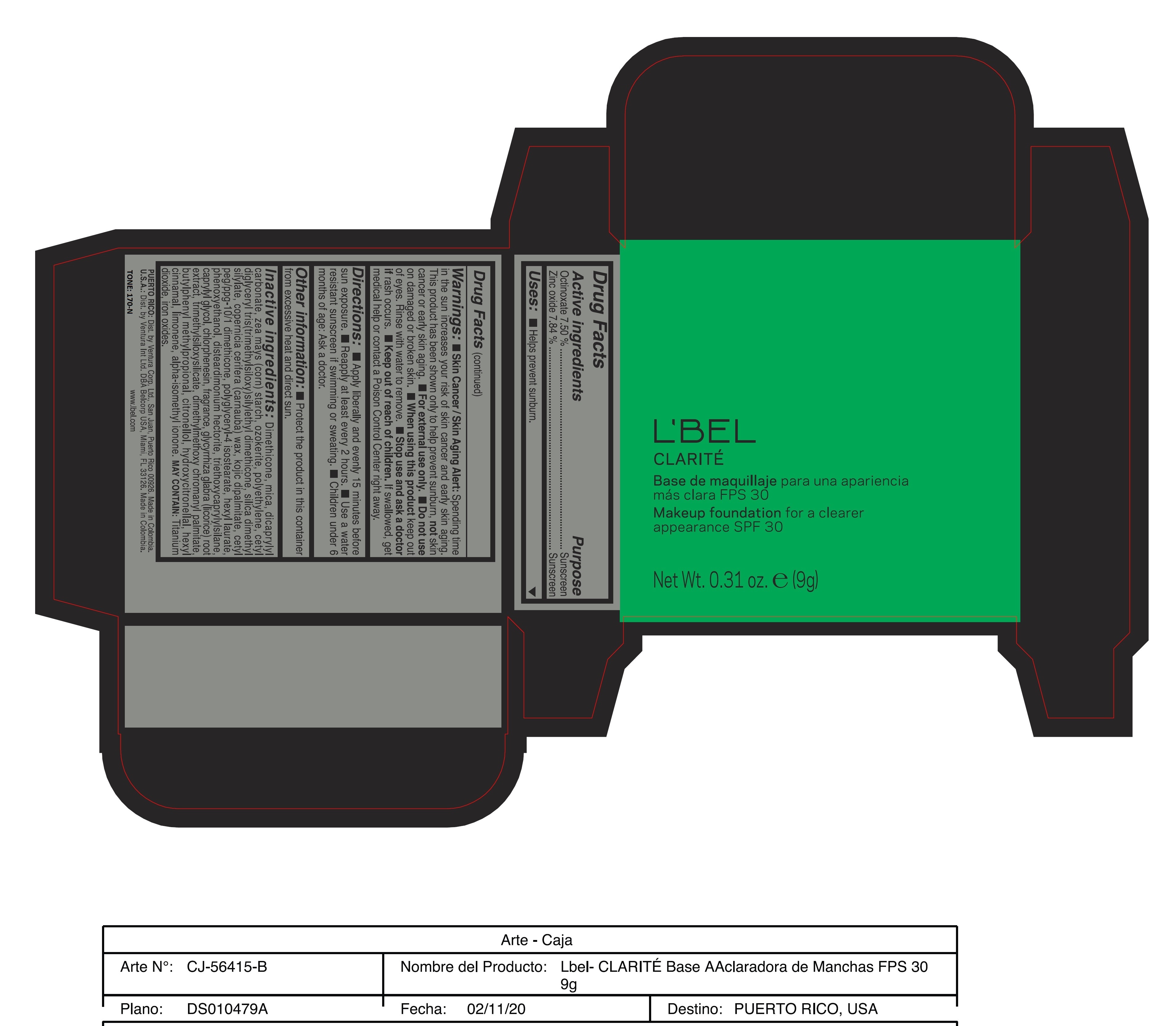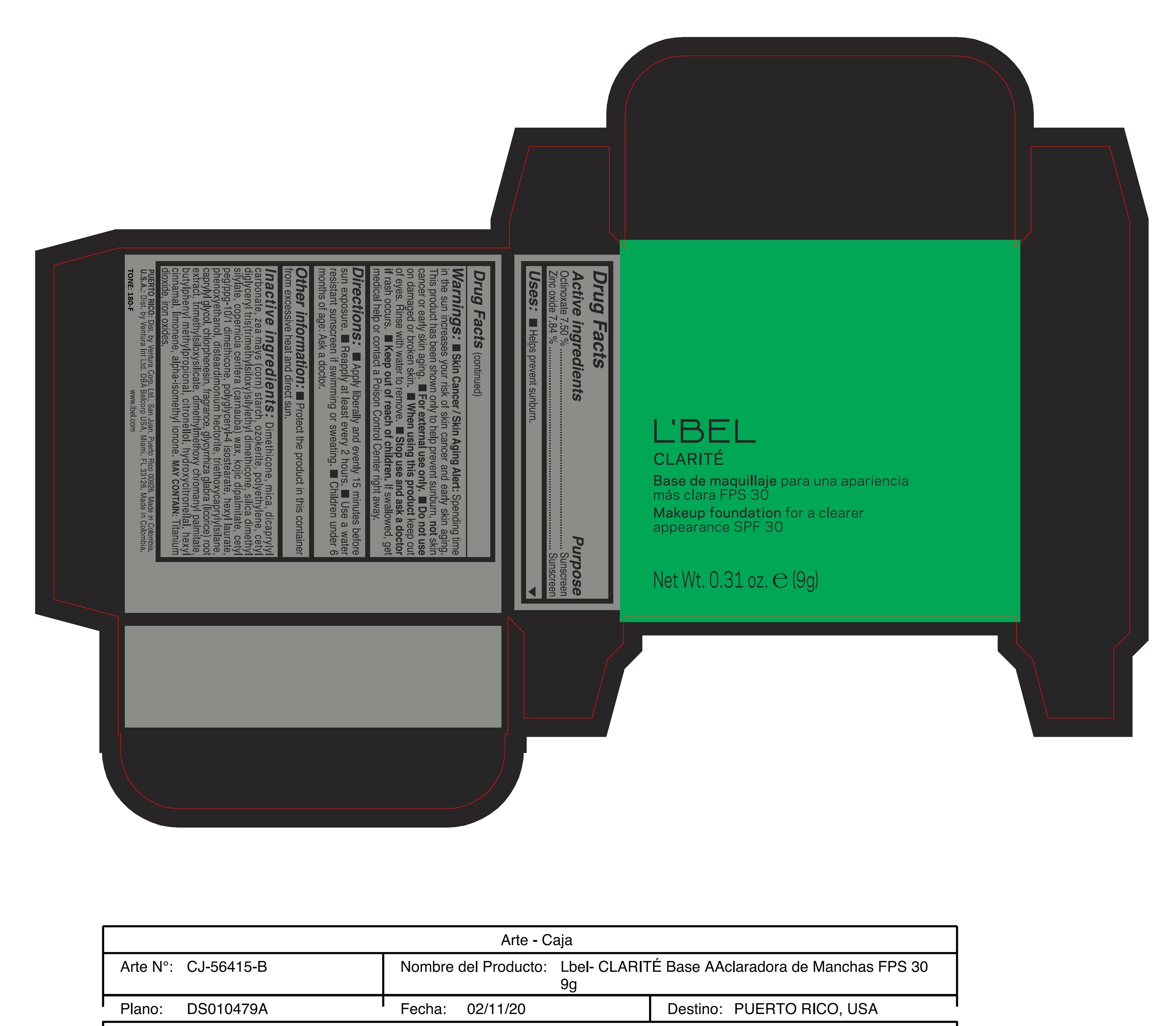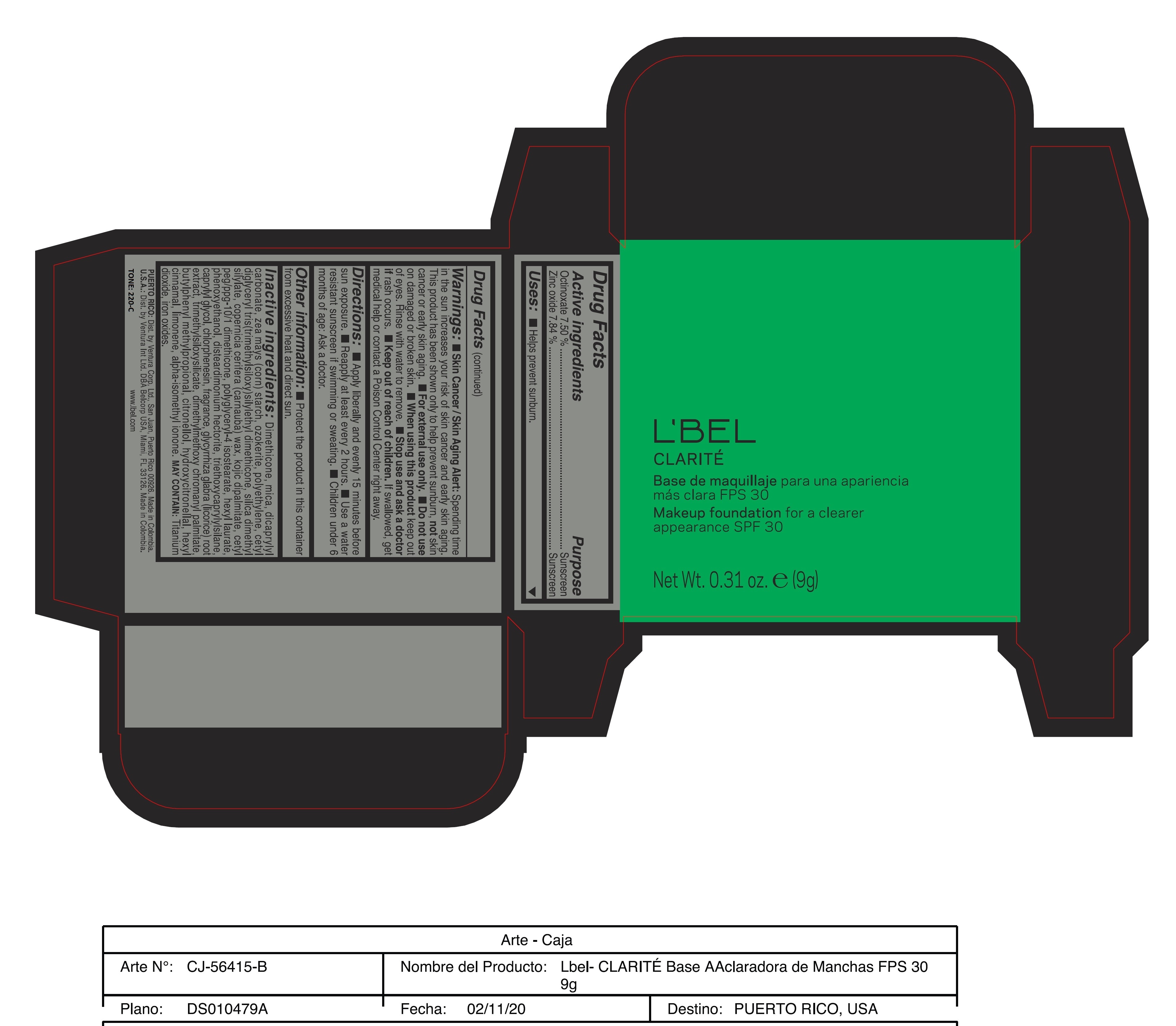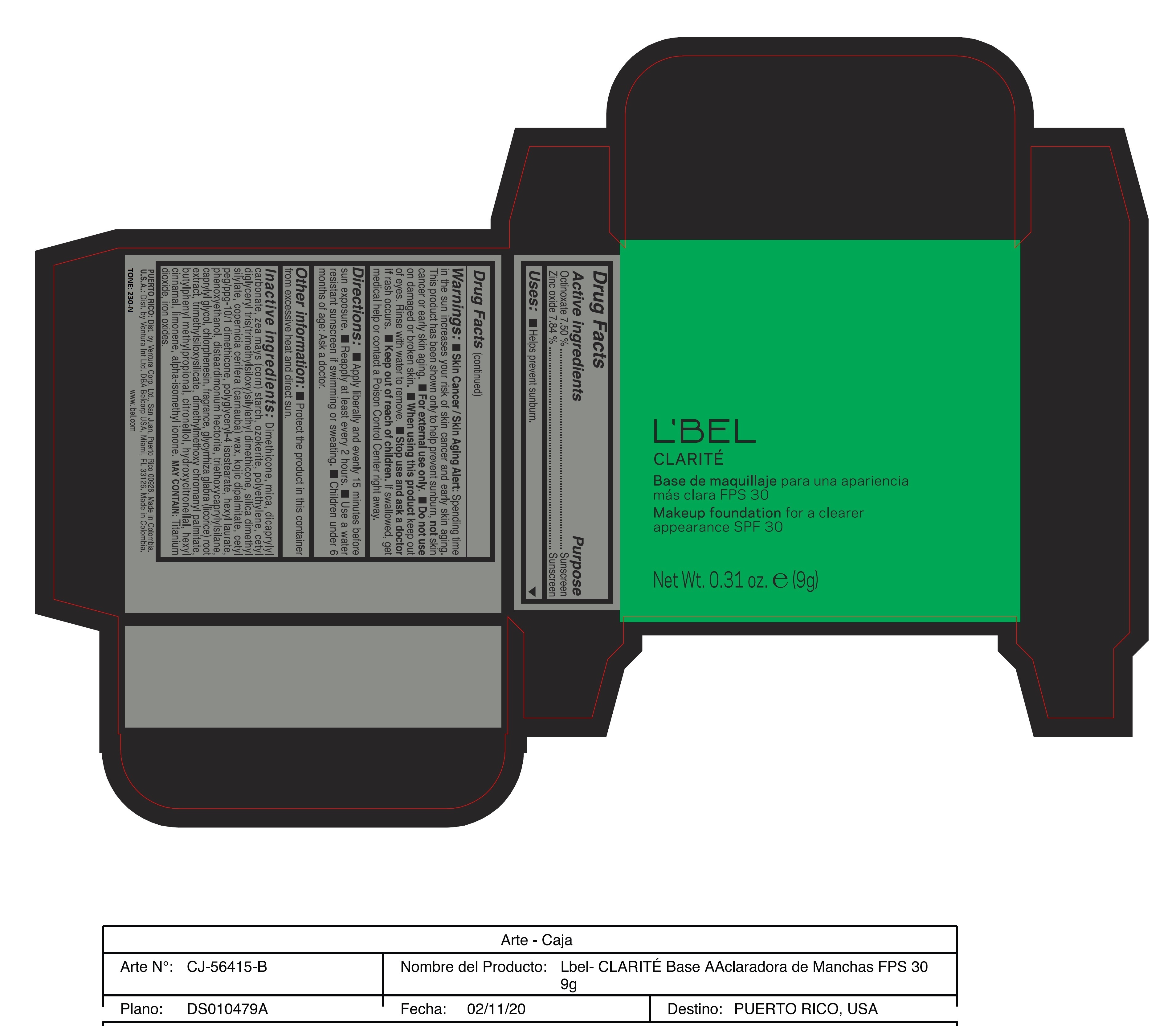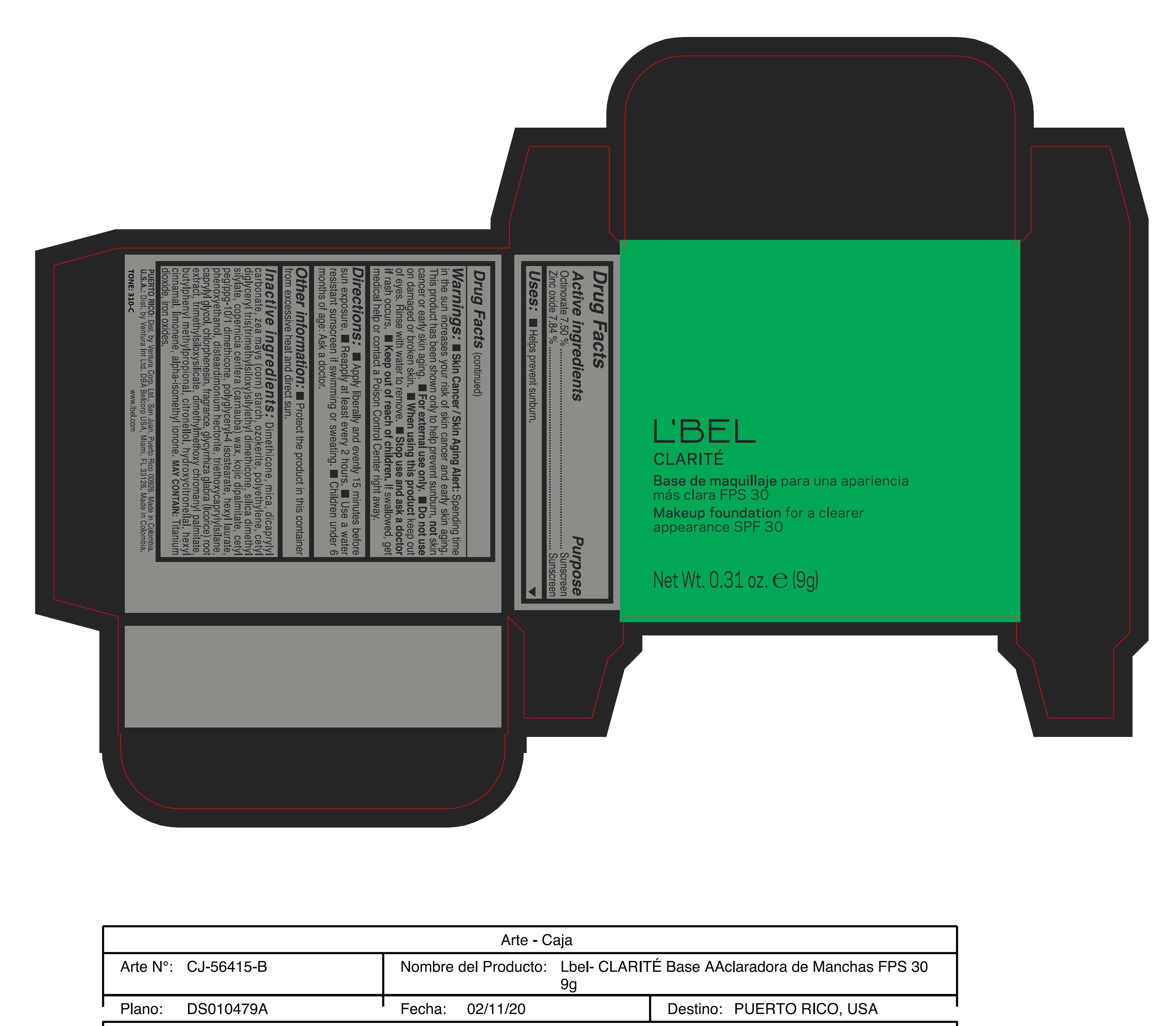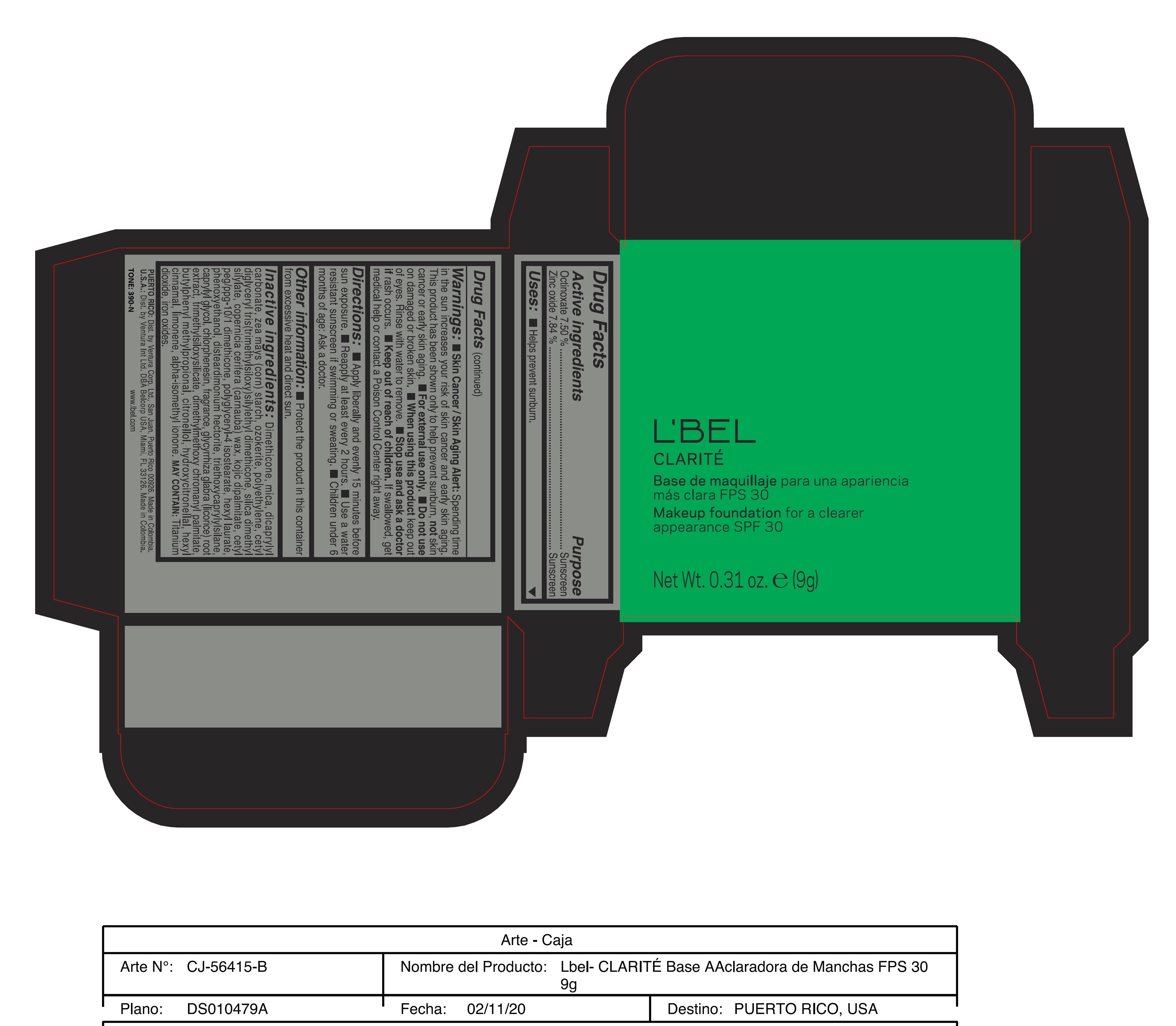 DRUG LABEL: Clarite Makeup Foundation for a Clearer Appearance SPF 30 390-N
NDC: 14141-212 | Form: PASTE
Manufacturer: BEL STAR S A
Category: otc | Type: HUMAN OTC DRUG LABEL
Date: 20251129

ACTIVE INGREDIENTS: OCTINOXATE 7.5 g/100 g; ZINC OXIDE 7.84 g/100 g
INACTIVE INGREDIENTS: DIMETHICONE; ISOMETHYL-.ALPHA.-IONONE; HIGH DENSITY POLYETHYLENE; POLYGLYCERYL-4 ISOSTEARATE; TRIETHOXYCAPRYLYLSILANE; DISTEARDIMONIUM HECTORITE; CHLORPHENESIN; BUTYLPHENYL METHYLPROPIONAL; HYDROXYCITRONELLAL; CETYL PEG/PPG-10/1 DIMETHICONE (HLB 2); PHENOXYETHANOL; .BETA.-CITRONELLOL, (R)-; TRIMETHYLSILOXYSILICATE (M/Q 0.8-1.0); .ALPHA.-HEXYLCINNAMALDEHYDE; LIMONENE, (+/-)-; FERRIC OXIDE YELLOW; MICA; DICAPRYLYL CARBONATE; STARCH, CORN; CERESIN; SILICA DIMETHYL SILYLATE; CARNAUBA WAX; KOJIC DIPALMITATE; HEXYL LAURATE; CAPRYLYL GLYCOL; GLYCYRRHIZA GLABRA; DIMETHYLMETHOXY CHROMANYL PALMITATE; FERRIC OXIDE RED; FERROSOFERRIC OXIDE

Clarite Makeup Foundation for a Clearer Appearance SPF 30

Active Ingredients Purpose

Octinoxate 7.50% Sunscreen

Zinc Oxide 7.84% Sunscreen

Uses

- Helps prevent sunburn

Keep out of reach of children.If swallowed, get medical help or contact a Poison Control Center right away

Stop use and ask a doctorif rash occurs.

Warnings:

Skin Cancer/Skin Aging Alert:Spending time in the sun increases your risk of skin cancer and early skin aging. This product has been shown only to help prevent sunburn, not skin cancer or early skin aging.
For external use only
Do not useon damaged or broken skin.
When using this product keep out of eyes. Rinse with water to remove.

Directions:

Apply Liberally and evenly 15 minutes before sun exposure
Reapply at least every 2 hours
Use a water resistant sunscreen if swimming or sweating
Children under six months of age: Ask a doctor

Other information:

Protect the product in this container from excessive hear and direct sun

INACTIVE INGREDIENT

Inactive ingredients:Dimethicone, mica, dicaprylyl carbonate, zea mays (corn) starch, ozokerite, polyethylene, cetyl diglyceryl tris(trimethylsiloxy)silylethyl dimethicone, silica dimethyl silylate, copernicia cerifera (carnauba) wax, kojic dipalmitate, cetyl peg/ppg-10/1 dimethicone, polyglyceryl-4 isostearate, hexyl laurate, phenoxyethanol, disteardimonium hectorite, triethoxycaprylylsilane, caprylyl glycol, chlorphenesin, fragrance, glycyrrhiza glabra (licorice) root extract, trimethylsiloxysilicate, dimethylmethoxy chromanyl palmitate, butylphenyl methylpropional, citronellol, hydroxycitronellal, hexyl cinnamal, limonene, alpha-isomethyl ionone.
may contain:titanium dioxide, iron oxides.

170-N

L'Bel CLARITE
Base de maquillaje para una apariencia mas clara FPS 30

Makeup foundation for a clearer appearance SPF 30 170-N
Net Wt. 0.31 oz. e (9g)

180-F

L'Bel CLARITE
Base de maquillaje para una apariencia mas clara FPS 30

Makeup foundation for a clearer appearance SPF 30 180-F
Net Wt. 0.31 oz. e (9g)

220-C

L'Bel CLARITE
Base de maquillaje para una apariencia mas clara FPS 30

Makeup foundation for a clearer appearance SPF 30 220-C
Net Wt. 0.31 oz. e (9g)

230-N

L'Bel CLARITE
Base de maquillaje para una apariencia mas clara FPS 30

Makeup foundation for a clearer appearance SPF 30 230-N
Net Wt. 0.31 oz. e (9g)

310-C

L'Bel CLARITE
Base de maquillaje para una apariencia mas clara FPS 30

Makeup foundation for a clearer appearance SPF 30 310-C
Net Wt. 0.31 oz. e (9g)

390-N

L'Bel CLARITE
Base de maquillaje para una apariencia mas clara FPS 30
Makeup foundation for a clearer appearance SPF 30 390-N
Net Wt. 0.31 oz. e (9g)